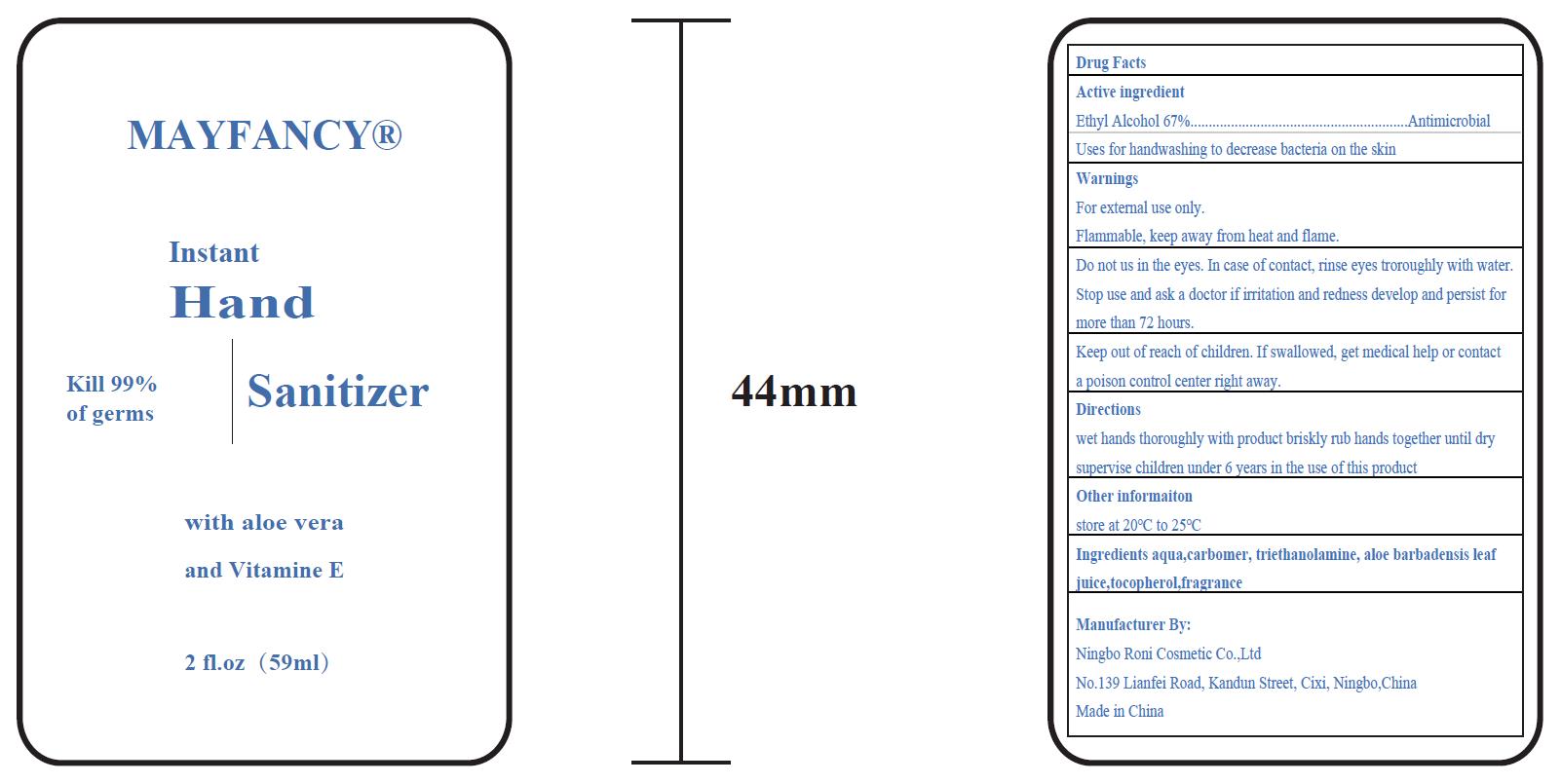 DRUG LABEL: Hand Sanitizer
NDC: 77309-101 | Form: GEL
Manufacturer: Ningbo Roni Cosmetic Co., Ltd
Category: otc | Type: HUMAN OTC DRUG LABEL
Date: 20200512

ACTIVE INGREDIENTS: ALCOHOL 43.365 mL/59 mL
INACTIVE INGREDIENTS: .GAMMA.-TOCOPHEROL; CARBOMER INTERPOLYMER TYPE A (ALLYL SUCROSE CROSSLINKED); WATER; ALOE VERA LEAF; TROLAMINE; CLOVE

Roni, Hand Sanitizer, Ethyl Alcohol 67% w/w, Gel, 59mL

Active Ingredient(s)

Ethyl Alcohol 67% w/w. Purpose: Antimicrobial

Purpose

Antimicrobial.

Use

Uses for handwashing to decrease bacteria on the skin.

Warnings

For external use only.

Flammable, keep away from heat and flame.

Do not use

Do not us in the eyes. In case of contact, rinse eyes troroughly with water.

When using this product, do not use in or near the eyes or wound.

Stop use and ask a doctor if irritation and redness develop and persist for more than 72 hours.

Keep out of reach of children. If swallowed, get medical help or contact a poison control center right away.

Directions

- Dispense product evenly on palms or on material surface and rub your hands until dry.
- Children should be under adult supervision when using this product.
- No dilute required.

Other information

Store at 20℃ to 25℃.

Inactive ingredients

Aqua, Carbomer, Triethanolamine, Aloe barbadensis leaf juice, Tocopherol, Fragrance.